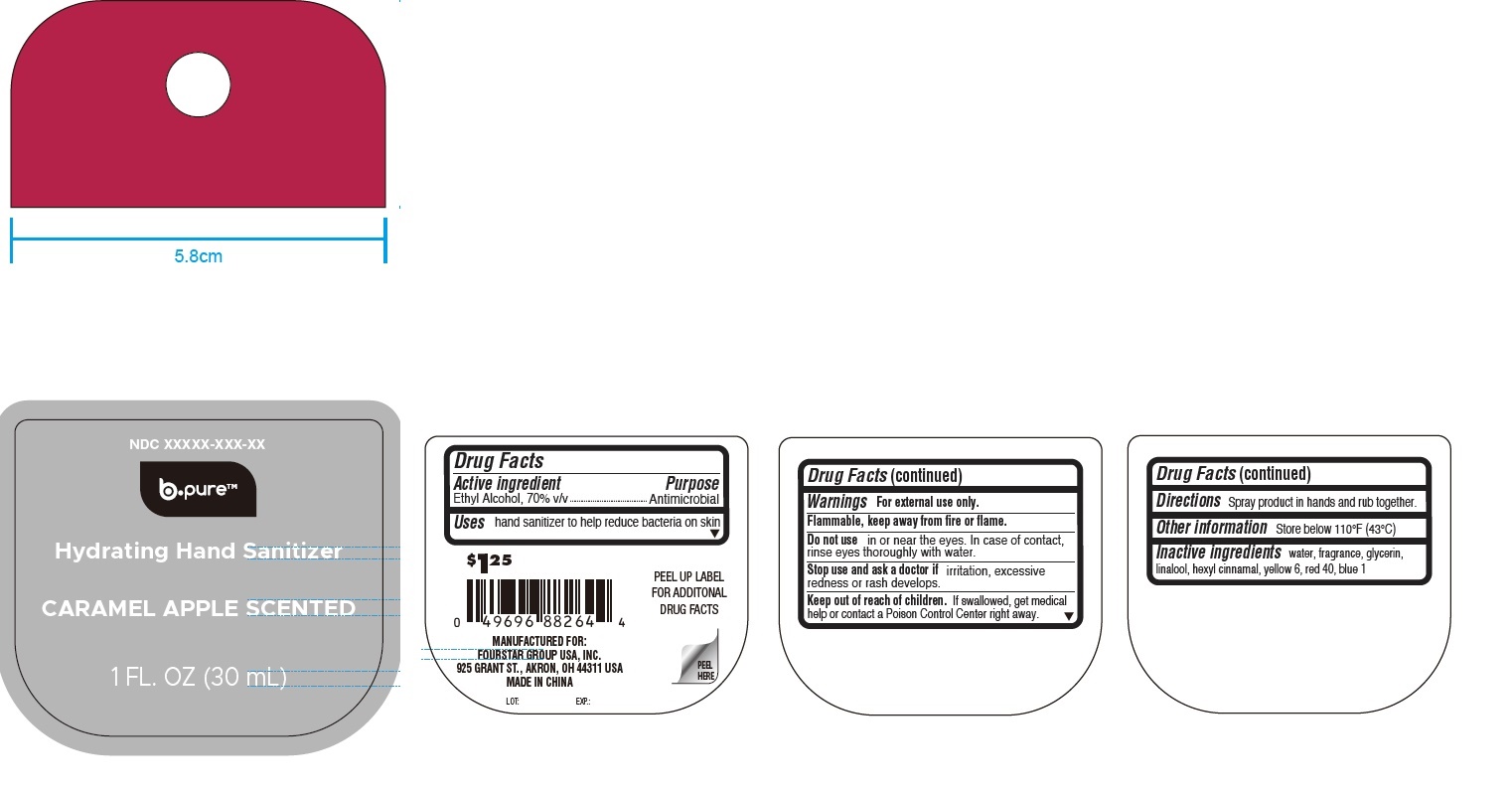 DRUG LABEL: b pure Hydrating Hand Sanitizer Caramel Apple Scented
NDC: 80684-107 | Form: LIQUID
Manufacturer: FOURSTAR GROUP USA, INC.
Category: otc | Type: HUMAN OTC DRUG LABEL
Date: 20240606

ACTIVE INGREDIENTS: ALCOHOL 70 mL/100 mL
INACTIVE INGREDIENTS: WATER; GLYCERIN; LINALOOL, (+/-)-; .ALPHA.-HEXYLCINNAMALDEHYDE; ISOMETHYL-.ALPHA.-IONONE; FD&C YELLOW NO. 6; FD&C RED NO. 40; FD&C BLUE NO. 1

b.pure Hydrating Hand Sanitizer, Caramel Apple Scented

Active ingredient

Ethyl Alcohol, 70% v/v

Purpose

Antimicrobial

Uses

hand sanitizer to help reduce bacteria on skin

Warnings

For external use only.

Flammable, keep away from fire or flame.

Do not use

in or near the eyes. In case of contact, rinse eyes thoroughly with water.

Stop use and ask a doctor if

irritation, excessive redness or rash develops.

Keep out of reach of c hildren.

If swallowed, get medical help or contact a Poison Control Center right away.

Directions

Spray product in hands and rub together.

Other information

Store below 110°F (43°C)

Inactive ingredients

water, fragrance, glycerin, linalool, hexyl cinnamal, yellow 6, red 40, blue 1